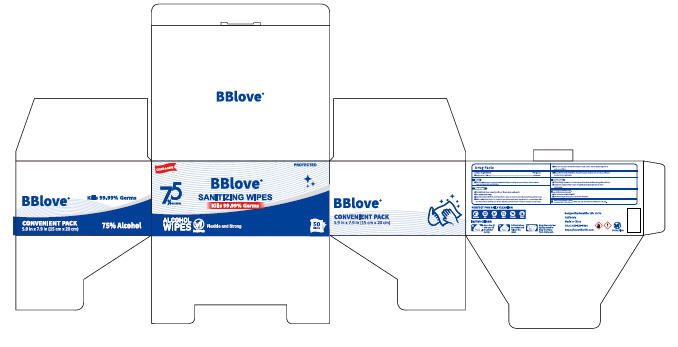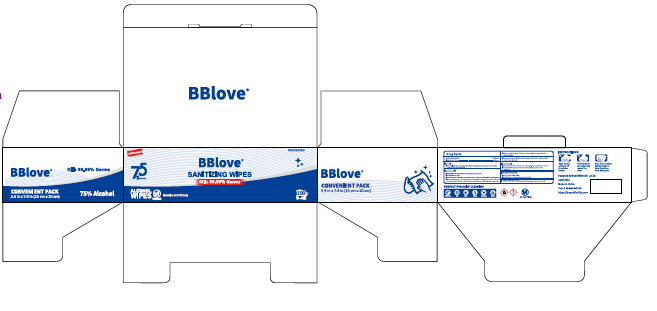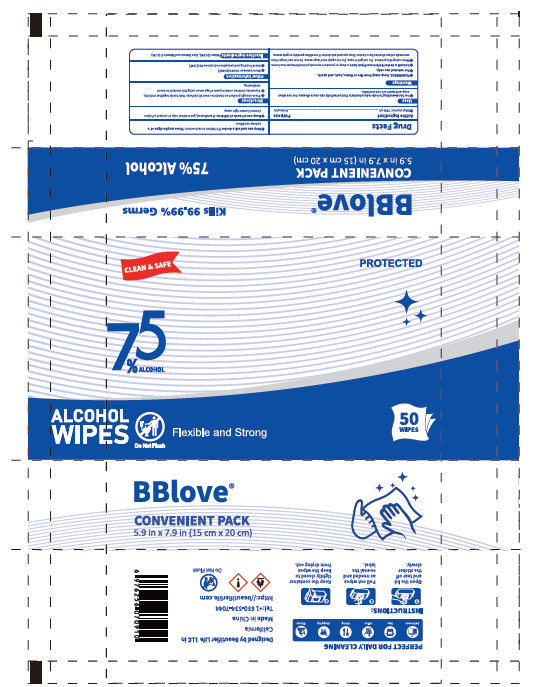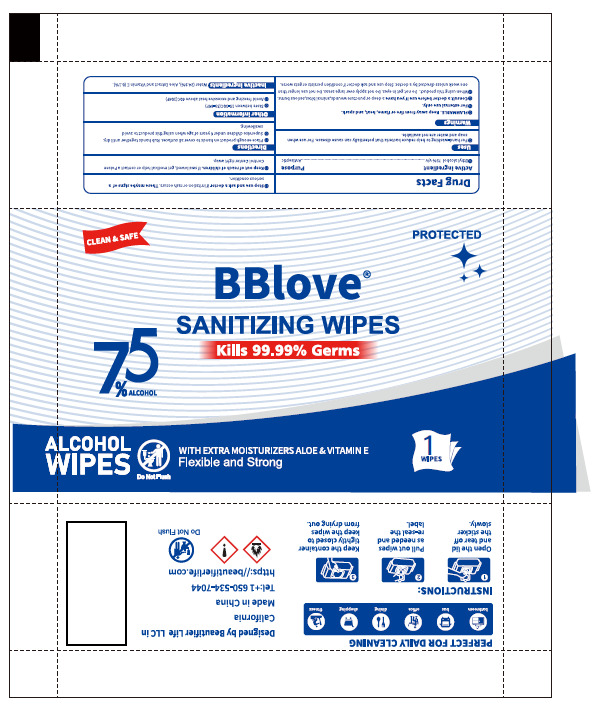 DRUG LABEL: BBlove ALCOHOL WIPES
NDC: 43116-038 | Form: CLOTH
Manufacturer: Shenzhen Shierjie Biological Engineering Co., LTD
Category: otc | Type: HUMAN OTC DRUG LABEL
Date: 20250331

ACTIVE INGREDIENTS: ALCOHOL 75 U/100 U
INACTIVE INGREDIENTS: WATER; ALOE; ALPHA-TOCOPHEROL

43116-038
BBlove ALCOHOL WIPES

Active Ingredient

Ethyl alcohol 75%

Purpose

Antiseptic

Use

For hand-washing to help reduce bacteria that potentially can cause disease. For use when
soap and water are not available.

Warnings

●FLAMMABLE. Keep away from fire or flame, heat, and spark.
●For external use only.
●Consult a doctor before use if you have a deep or puncture wounds,animal bites,serious burns.
●When using this product. Do not get in eyes. Do not apply over large areas. Do not use longer than
one week unless directed by a doctor. Stop use and ask doctor if condition persists or gets worse.

Do not use

When using this product. Do not get in eyes. Do not apply over large areas. Do not use longer than
one week unless directed by a doctor. Stop use and ask doctor if condition persists or gets worse.

When Using

When using this product. Do not get in eyes. Do not apply over large areas. Do not use longer than
one week unless directed by a doctor. Stop use and ask doctor if condition persists or gets worse.

Stop Use

Stop use and ask a doctor if irritation or rash occurs. These maybe signs of a
serious condition.

Keep Oot Of Reach Of Children

Keep out of reach of children. If swallowed, get medical help or contact a Poison
Control Center right away.

Directions

●Place enough product on hands to cover all surfaces. Rub hands together until dry.
●Supervise children under 6 years of age when using this product to avoid swallowing.

Other information

●Store between 15-30C(59-86F)
●Avoid freezing and excessive heat above 40C(104F)

Inactive ingredients

Water (24.9%), Aloe Extract and Vitamin E (0.1%).